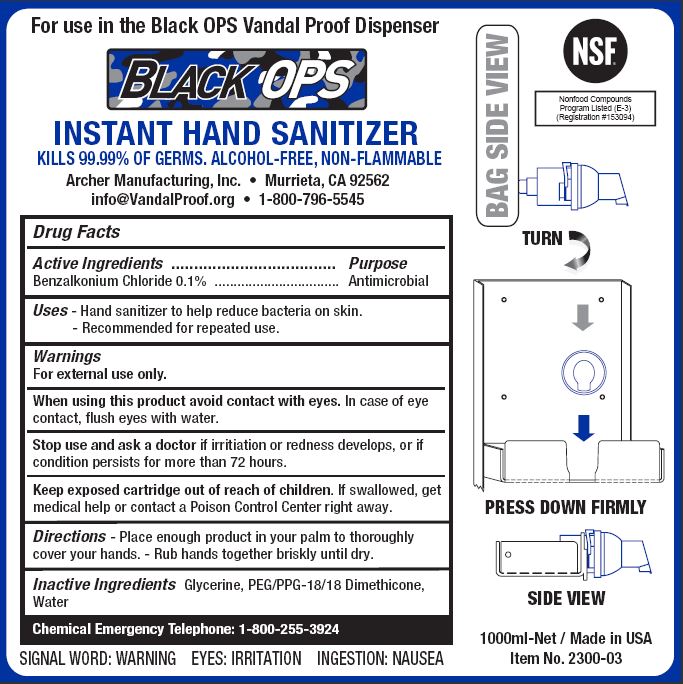 DRUG LABEL: BLACK OPS INSTANT HAND SANITIZER
NDC: 79016-104 | Form: SOLUTION
Manufacturer: Archer Manufacturing, Inc.
Category: otc | Type: HUMAN OTC DRUG LABEL
Date: 20241205

ACTIVE INGREDIENTS: BENZALKONIUM CHLORIDE 0.1 g/100 mL
INACTIVE INGREDIENTS: GLYCERIN; WATER; PEG/PPG-18/18 DIMETHICONE

ARCHER - BLACK OPS INSTANT HAND SANITIZER (79016-104)

ACTIVE INGREDIENTS

BENZALKONIUM CHLORIDE 0.1%

PURPOSE

ANTIMICROBIAL

USES

- HAND SANITIZER TO HELP REDUCE BACTERIA ON THE SKIN.
- RECOMMENDED FOR REPEATED USE.

WARNINGS

FOR EXTERNAL USE ONLY.

WHEN USING THIS PRODUCT AVOID CONTACT WITH EYES. IN CASE OF EYE CONTACT, FLUSH WITH WATER.

STOP USE AND ASK A DOCTOR IF IRRITATION OR REDNESS DEVELOPS, OR IF CONDITION PERSISTS FOR MORE THAN 72 HOURS.

KEEP OUT OF REACH OF CHILDREN

KEEP EXPOSED CARTRIDGE OUT OF REACH OF CHILDREN. IF SWALLOWED, GET MEDICAL HELP OR CONTACT POISON CONTROL RIGHT AWAY.

DIRECTIONS

- Place enough product in your palm to thoroughly cover your hands.
- Rub hands together briskly until dry.

INACTIVE INGREDIENTS

Glycerine, PEG/PPG-18/18 Dimethicone, Water